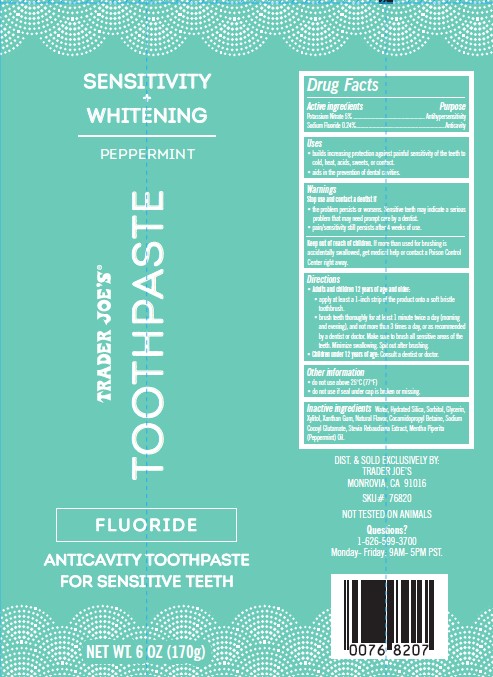 DRUG LABEL: Trader Joes
NDC: 71270-110 | Form: PASTE
Manufacturer: TRADER JOE'S COMPANY
Category: otc | Type: HUMAN OTC DRUG LABEL
Date: 20251008

ACTIVE INGREDIENTS: SODIUM FLUORIDE 2.4 mg/1 g; POTASSIUM NITRATE 50 mg/1 g
INACTIVE INGREDIENTS: WATER; HYDRATED SILICA; SORBITOL; GLYCERIN; COCAMIDOPROPYL BETAINE; PEPPERMINT OIL; XYLITOL; SODIUM COCOYL GLUTAMATE; STEVIA REBAUDIUNA LEAF; XANTHAN GUM

Trader Joe's Anticavity/ Antihypersensitivity Toothpaste

Active ingredients

- Potassium Nitrate .......... 5%
- Sodium Fluoride ............ 0.24%

Purposes

- Anti-hypersensitivity
- Anticavity

Uses

- builds increasing protection against painful sensitivity of the teeth to

cold, heat, acids, sweets, or contact.

- aids in the prevention of dental cavities.

Warnings

Stop use and contact a dentist if

- the problem persists or worsens. Sensitive teeth may indicate a serious

problem that may need prompt care by a dentist.

- pain/sensitivity still persists after 4 weeks of use.

Keep out of reach of children.

If more than used for brushing is accidentally swallowed, get medical help or contact a Poison Control
Center right away.

Directions

- Adults and children 12 years of age and older:
  - apply at least a 1-inch strip of the product onto a soft bristle

toothbrush.

- brush teeth thoroughly for at least 1 minute twice a day (morning

and evening), and not more than 3 times a day, or as recommended
by a dentist or doctor. Make sure to brush all sensitive areas of the
teeth. Minimize swallowing. Spit out after brushing.

- Children under 12 years of age: Consult a dentist or doctor.

Other information

- do not use above 25°C (77°F)
- do not use if seal under cap is broken or missing.

Inactive ingredients

Water, Hydrated Silica, Sorbitol, Glycerin, Xylitol, Xanthan Gum, Natural Flavor, Cocamidopropyl Betaine, Sodium
Cocoyl Glutamate, Stevia Rebaudiana Extract, Mentha Piperita (Peppermint) Oil.